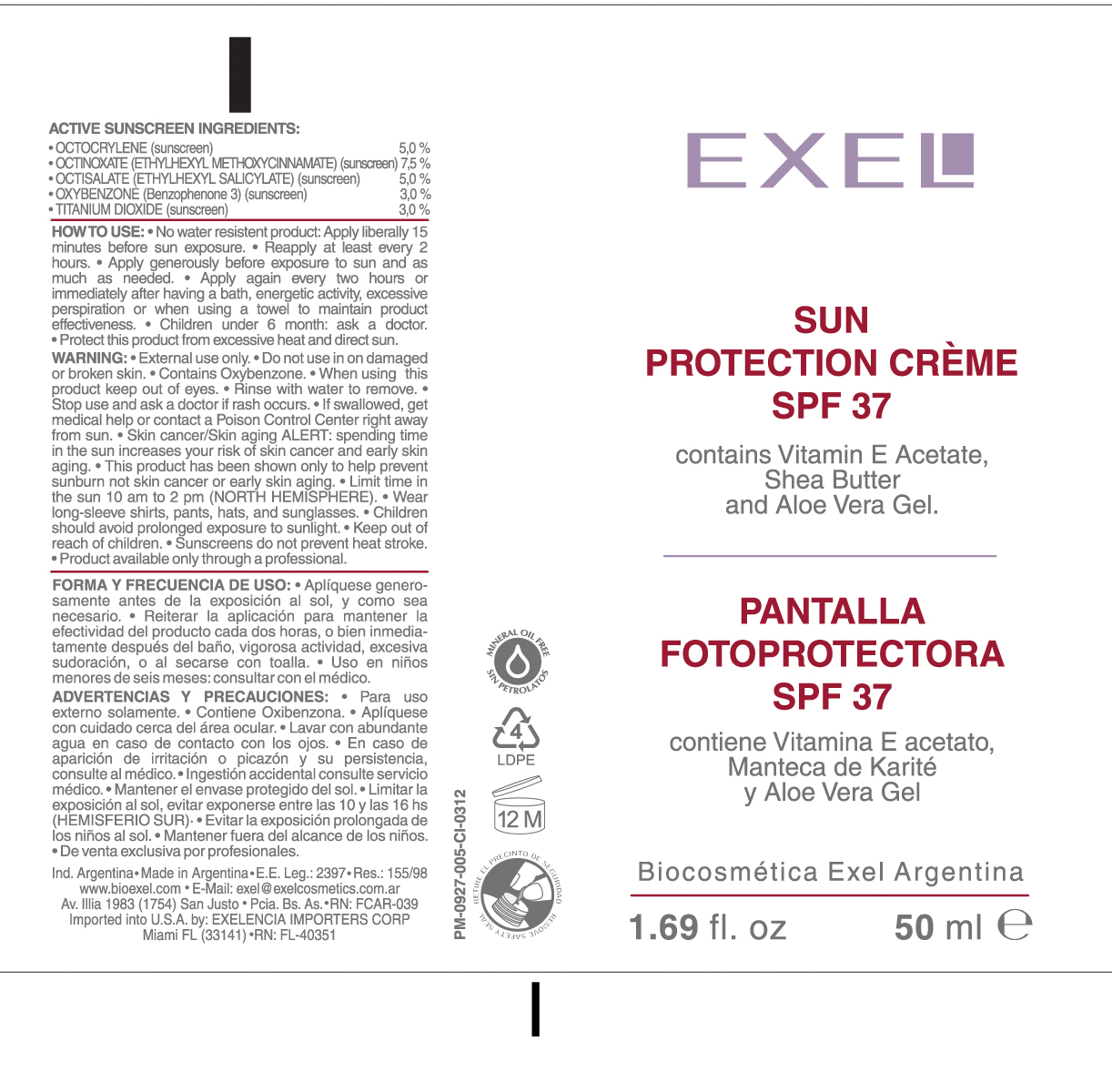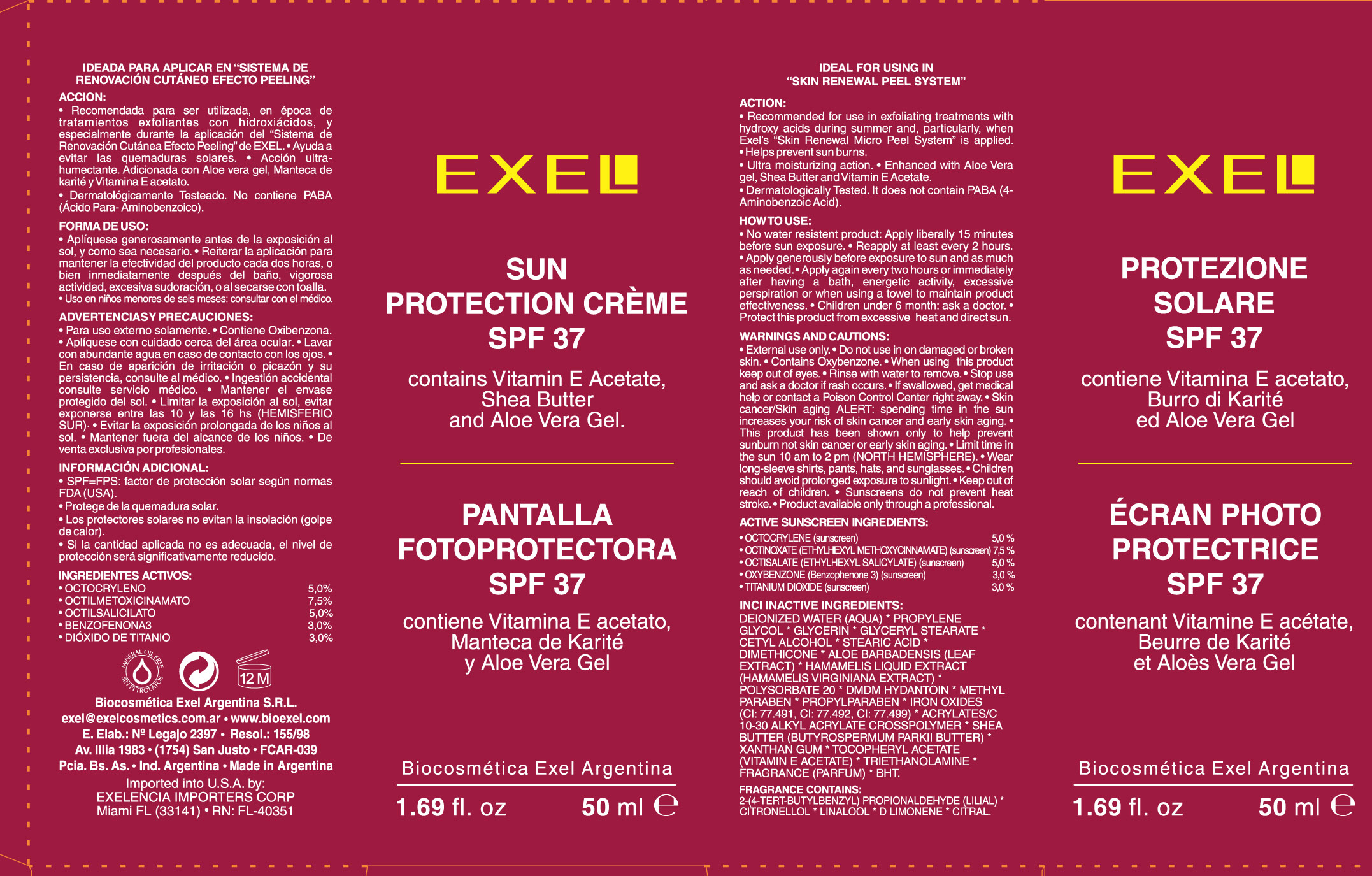 DRUG LABEL: 
                           
NDC: 53863-120 | Form: CREAM
Manufacturer: Exelencia Importers Corp
Category: otc | Type: HUMAN OTC DRUG LABEL
Date: 20121105

ACTIVE INGREDIENTS: OCTOCRYLENE 5 g/100 mL; OCTINOXATE 7.5 g/100 mL; OCTISALATE 5 g/100 mL; OXYBENZONE 3 g/100 mL; TITANIUM DIOXIDE 3 g/100 mL
INACTIVE INGREDIENTS: WATER; PROPYLENE GLYCOL; GLYCERIN; GLYCERYL MONOSTEARATE; CETYL ALCOHOL; STEARIC ACID; DIMETHICONE; ALOE VERA LEAF; HAMAMELIS VIRGINIANA TOP; POLYSORBATE 20; DMDM HYDANTOIN; METHYLPARABEN; PROPYLPARABEN; FERRIC OXIDE RED; FERRIC OXIDE YELLOW; FERROSOFERRIC OXIDE; CARBOMER INTERPOLYMER TYPE A (ALLYL SUCROSE CROSSLINKED); SHEA BUTTER; XANTHAN GUM; .ALPHA.-TOCOPHEROL ACETATE; TROLAMINE; BUTYLATED HYDROXYTOLUENE

Sun Protection creme SPF 37

Active Sunscreen Ingredients

Octocrylene (sunscreen) 5,0%

Octinoxate (Ethylhexyl Methoxy cinnamate) (sunscreen) 7,5%

Octisalate (Ethylhexyl Salicylate) (sunscreen) 5,0%

Oxybezone (Benzophenone 3) (sunscreen) 3,0%

Titanium Dioxide (sunscreen) 3,0%

PURPOSE

Action:

recommend for use in exfoliating treatments with hydroxy acids during summer and, perticularly, when Exel's "Skin Renewal Micro Peel System" is applied.

Helps prevent sunburn

Ultra moisturizing action. Enhanced with Aloe Vera gel, Shea Butter and Vitamin E Acetate.

Dermatologically tested. It does not contain PABA (4-Aminobenzoic Acid).

Keep out of reach of children.

Stop use if and ask a doctor if rash occurs. If swallowed get medical help or contact a poison control center right away.

WARNINGS

External use only.

Do not use in on damaged or broken skin.

Contains Oxybenzone.

When using this product, keep out of eyes.

Skin cancer/ Skin aging alert:

Spending time in the sun increases your risk of skin cancer and early skin aging.

This product has been shown only to prevent sunburn and not skin cancer and early skin aging.

Limit time in the sun 10 am to 2 p (North Hemisphere).

Wear long-sleeve shirts, pants, hats and sunglasses.

Children should avoid prolonged exposure to sunlight.

Sunscreens do not prevent heat stroke.

Product only available through a professional.

DOSAGE AND ADMINISTRATION

How to use

No water resistant product: Apply Liberally 15 minutes before sun exposure.

Reapply at least every two hours. Apply generously before exposure to sun as much as needed. Apply again every 2 hours or immediately after having a bath, energetic activity, excessive perspiration or when using a towel to maintain product effectiveness.

Children under 6 months: ask a doctor.

Protect this product from excessive heat and sunlight.

INCI Inactive Ingredients

Deionized Water (aqua) * Propylene Glycol * Glycerin * Glyceryl Stearate * Cetyl Alcohol * Stearic Acid * Dimethicone * Aloe Barbadensis (Leaf Extract) * Hamamelis Liquid Extract (Hamamelis Virginiana Extract) * Polysorbate 20 * DMDM Hydantoin
* Methylparaben * propylparaben * Iron Oxides (CI:77.491, CI:77.492, CI 77.499) * Acrylates/C10-30 Alkyl Acrylate Crosspolymer * Shea butter (Butyrospermum Parkii Butter) * Xanthan Gum * Tocopheryl Acetate (vitamin E acetate) * Triethanolamine
* Fragrance (Parfum) * BHT.

PACKAGE LABEL

Exel

Sun Protection Creme SPF

contains Vitamin E Acetate, Shea Butter, and Aloe Vera Gel.

1.69 fl. oz 50